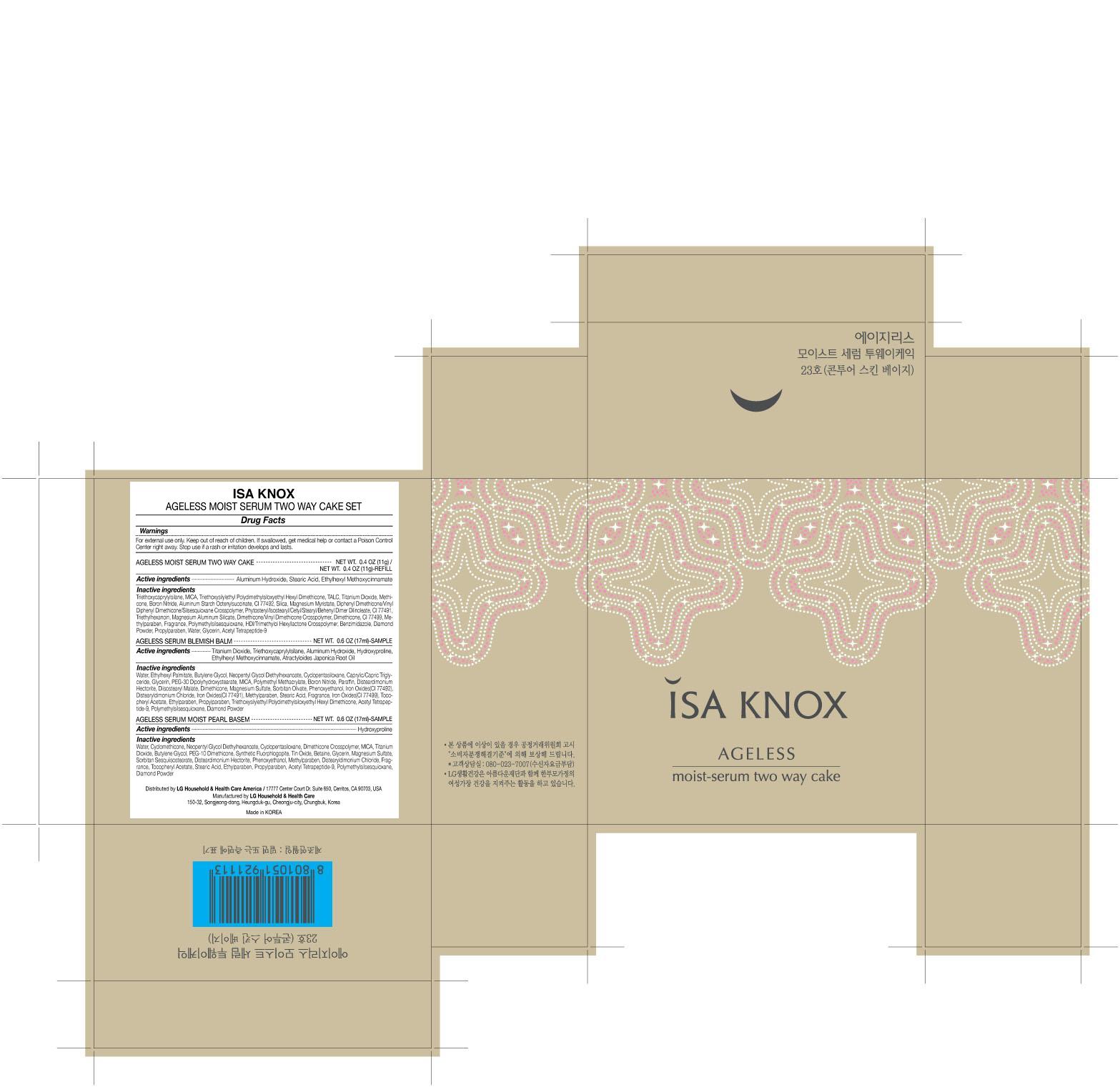 DRUG LABEL: ISA KNOX AGELESS MOIST SERUM TWO WAY CAKE 23
NDC: 53208-512 | Form: POWDER
Manufacturer: LG Household and Healthcare, Inc.
Category: otc | Type: HUMAN OTC DRUG LABEL
Date: 20120620

ACTIVE INGREDIENTS: TITANIUM DIOXIDE 13.38 g/100 g; OCTINOXATE 4 g/100 g
INACTIVE INGREDIENTS: TALC; TRIETHOXYCAPRYLYLSILANE; MICA; BORON NITRIDE; ALUMINUM HYDROXIDE; METHYLPARABEN; PROPYLPARABEN; DIMETHICONE; STEARIC ACID; ALUMINUM STARCH OCTENYLSUCCINATE; FERRIC OXIDE YELLOW; SILICON DIOXIDE; MAGNESIUM MYRISTATE; FERRIC OXIDE RED; TRIETHYLHEXANOIN; MAGNESIUM ALUMINUM SILICATE; FERROSOFERRIC OXIDE; BENZNIDAZOLE; GLYCERIN; ACETYL TETRAPEPTIDE-9

Drug Fact

ACTIVE INGREDIENT

TITANIUM DIOXIDE 13.38g/100g

OCTINOXATE 4g/100g

WARNINGS AND PRECAUTIONS

For external use only.

Keep out of reach of children. Is swallowed, get medical help or contact a Poison Control Center right away.

WHEN USING

Keep out of eyes. Rinse with water to remove.